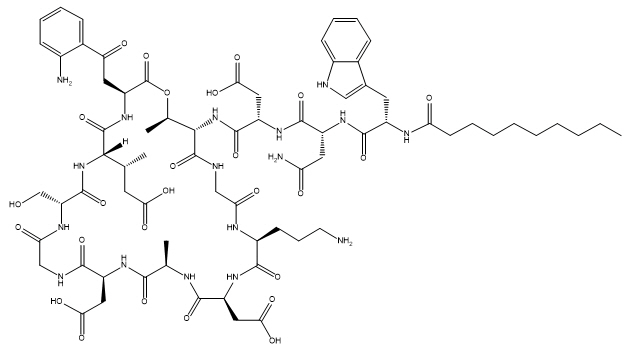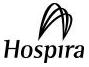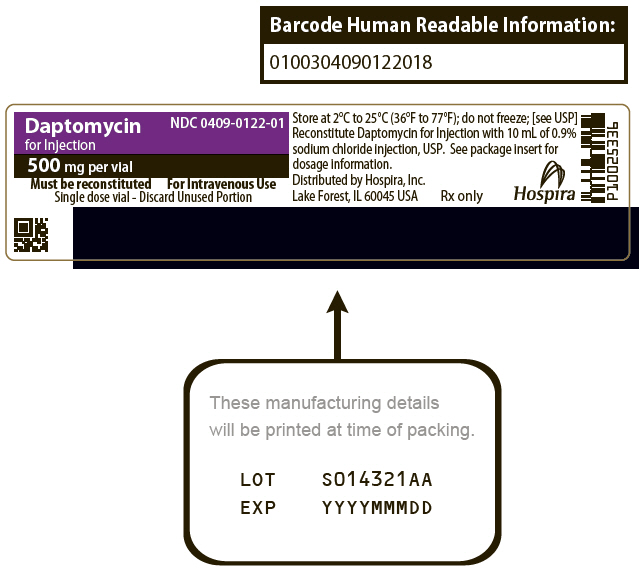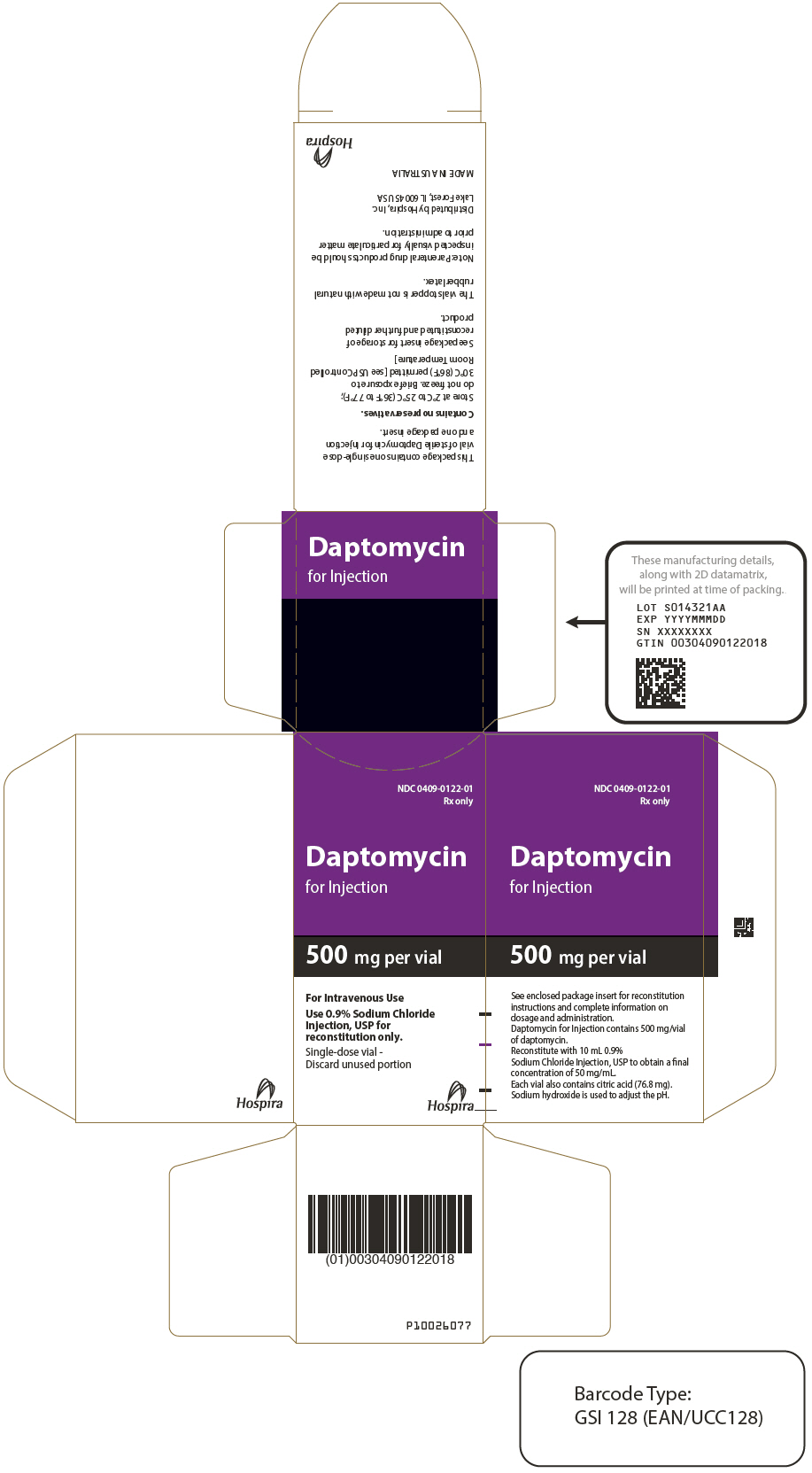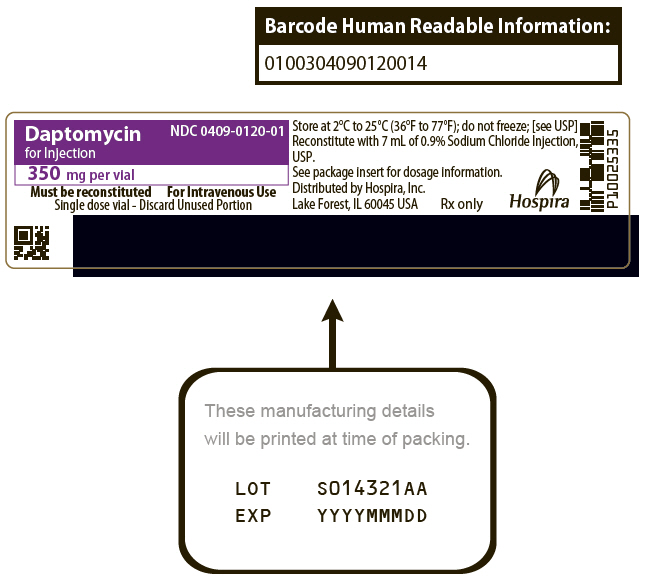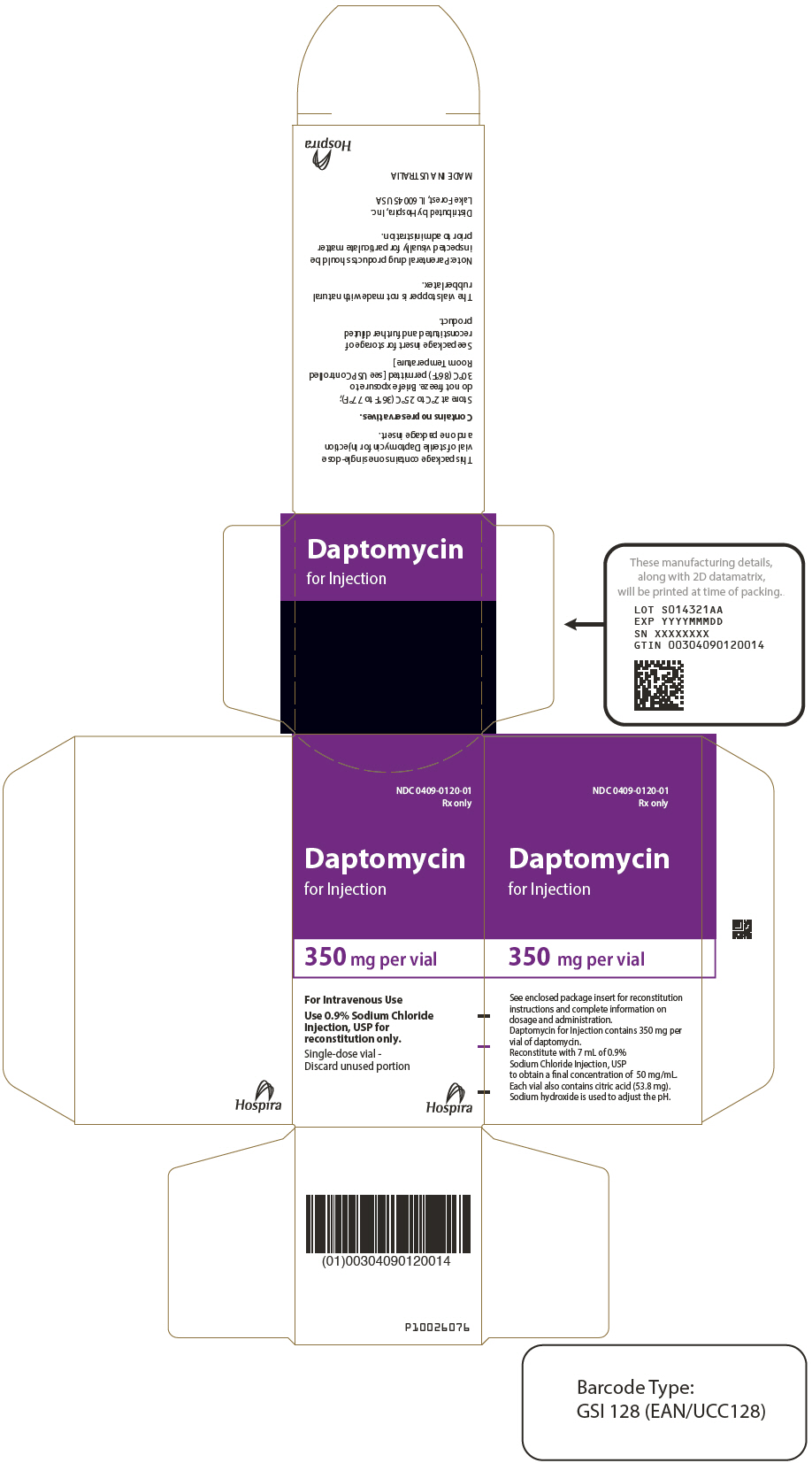 DRUG LABEL: Daptomycin
NDC: 0409-0122 | Form: INJECTION, POWDER, LYOPHILIZED, FOR SOLUTION
Manufacturer: Hospira, Inc.
Category: prescription | Type: HUMAN PRESCRIPTION DRUG LABEL
Date: 20250227

ACTIVE INGREDIENTS: DAPTOMYCIN 500 mg/10 mL
INACTIVE INGREDIENTS: SODIUM HYDROXIDE; ANHYDROUS CITRIC ACID

HIGHLIGHTS OF PRESCRIBING INFORMATION

These highlights do not include all the information needed to use DAPTOMYCIN FOR INJECTION safely and effectively. See full prescribing information for DAPTOMYCIN FOR INJECTION.
DAPTOMYCIN for injection, for intravenous use
Initial U.S. Approval: 2003

1 INDICATIONS AND USAGE

Daptomycin for Injection is a lipopeptide antibacterial indicated for the treatment of:

- Complicated skin and skin structure infections (cSSSI) in adult patients (1.1) and,
- Staphylococcus aureus bloodstream infections (bacteremia), in adult patients including those with right-sided infective endocarditis, (1.2)

Limitations of Use:

- This Daptomycin for Injection product is not approved for use in pediatric patients. (1.3)
- Daptomycin for Injection is not indicated for the treatment of pneumonia. (1.3)
- Daptomycin for Injection is not indicated for the treatment of left-sided infective endocarditis due to S. aureus. (1.3)
- Daptomycin for Injection is not recommended in pediatric patients younger than one year of age due to the risk of potential effects on muscular, neuromuscular, and/or nervous systems (either peripheral and/or central) observed in neonatal dogs. (1.3)

To reduce the development of drug-resistant bacteria and maintain the effectiveness of Daptomycin for Injection and other antibacterial drugs, Daptomycin for Injection should be used to treat or prevent infections that are proven or strongly suspected to be caused by bacteria. (1.4)

2 DOSAGE AND ADMINISTRATION

Adult Patients

- Administer to adult patients intravenously in 0.9% sodium chloride, either by injection over a 2-minute period or by infusion over a 30-minute period. (2.1, 2.5)
- Recommended dosage regimen for adult patients (2.2, 2.3, 2.4):

Creatinine Clearance (CrCl) | Dosage Regimen
Creatinine Clearance (CrCl) | cSSSI For 7 to 14 days | S. aureus Bacteremia For 2 to 6 weeks
≥30 mL/min | 4 mg/kg once every 24 hours | 6 mg/kg once every 24 hours
<30 mL/min, including hemodialysis and CAPD | 4 mg/kg once every 48 hours [Administered following hemodialysis on hemodialysis days.] | 6 mg/kg once every 48 hours

- There are other formulations of daptomycin that have differences concerning storage and reconstitution. Carefully follow the reconstitution and storage procedures described in this labeling. (2.5)
- Do not use in conjunction with ReadyMED® elastomeric infusion pumps in adult patients. (2.5)

3 DOSAGE FORMS AND STRENGTHS

- 350 mg lyophilized powder for reconstitution in a single-dose vial (3)
- 500 mg lyophilized powder for reconstitution in a single-dose vial (3)

4 CONTRAINDICATIONS

Known hypersensitivity to daptomycin (4)

5 WARNINGS AND PRECAUTIONS

- Anaphylaxis/hypersensitivity reactions (including life-threatening): Discontinue Daptomycin for Injection and treat sign/symptoms. (5.1)
- Myopathy and rhabdomyolysis: Monitor CPK levels and follow muscle pain or weakness; if elevated CPK or myopathy occurs, consider discontinuation of Daptomycin for Injection. (5.2)
- Eosinophilic pneumonia: Discontinue Daptomycin for Injection and consider treatment with systemic steroids. (5.3)
- Drug Reaction with Eosinophilia and Systemic Symptoms (DRESS): Discontinue Daptomycin for Injection and institute appropriate treatment. (5.4)
- Tubulointerstitial Nephritis (TIN): Discontinue Daptomycin for Injection and institute appropriate treatment. (5.5)
- Peripheral neuropathy: Monitor for neuropathy and consider discontinuation. (5.6)
- Potential nervous system and/or muscular system effects in pediatric patients younger than 12 months: Avoid use of Daptomycin for Injection in this age group. (5.7)
- Clostridioides difficile–associated diarrhea: Evaluate patients if diarrhea occurs. (5.8)
- Persisting or relapsing S. aureus bacteremia/endocarditis: Perform susceptibility testing and rule out sequestered foci of infection. (5.9)
- Decreased efficacy was observed in adult patients with moderate baseline renal impairment. (5.10)

6 ADVERSE REACTIONS

- Adult cSSSI Patients: The most common adverse reactions that occurred in ≥2% of adult cSSSI patients receiving daptomycin for injection 4 mg/kg were diarrhea, headache, dizziness, rash, abnormal liver function tests, elevated creatine phosphokinase (CPK), urinary tract infections hypotension, and dyspnea. (6.1)
- Adult S. aureus bacteremia/endocarditis Patients: The most common adverse reactions that occurred in ≥5% of S. aureus bacteremia/endocarditis patients receiving daptomycin for injection 6 mg/kg were sepsis, bacteremia, abdominal pain, chest pain, edema, pharyngolaryngeal pain, pruritus, increased sweating, insomnia, elevated CPK, and hypertension. (6.1)

To report SUSPECTED ADVERSE REACTIONS, contact Hospira at 1-800-438-1985 or FDA at 1-800-FDA-1088 or www.fda.gov/medwatch.

FULL PRESCRIBING INFORMATION

1 INDICATIONS AND USAGE

1.1 Complicated Skin and Skin Structure Infections (cSSSI)

Daptomycin for Injection is indicated for the treatment of adult patients with complicated skin and skin structure infections (cSSSI) caused by susceptible isolates of the following Gram-positive bacteria: Staphylococcus aureus (including methicillin-resistant isolates), Streptococcus pyogenes, Streptococcus agalactiae, Streptococcus dysgalactiae subsp. equisimilis, and Enterococcus faecalis (vancomycin-susceptible isolates only).

1.2 Staphylococcus aureus Bloodstream Infections (Bacteremia) in Adult Patients, Including Those with Right-Sided Infective Endocarditis, Caused by Methicillin-Susceptible and Methicillin-Resistant Isolates

Daptomycin for Injection is indicated for the treatment of adult patients with Staphylococcus aureus bloodstream infections (bacteremia), including adult patients with right-sided infective endocarditis, caused by methicillin-susceptible and methicillin-resistant isolates.

1.3 Limitations of Use

This Daptomycin for Injection product is not approved for use in pediatric patients [see Use in Specific Populations (8.4)].

Daptomycin for Injection is not indicated for the treatment of pneumonia.

Daptomycin for Injection is not indicated for the treatment of left-sided infective endocarditis due to S. aureus. The clinical trial of daptomycin for injection in adult patients with S. aureus bloodstream infections included limited data from patients with left-sided infective endocarditis; outcomes in these patients were poor [see Clinical Studies (14.2)]. Daptomycin for Injection has not been studied in patients with prosthetic valve endocarditis.

Daptomycin for Injection is not recommended in pediatric patients younger than 1 year of age due to the risk of potential effects on muscular, neuromuscular, and/or nervous systems (either peripheral and/or central) observed in neonatal dogs [see Warnings and Precautions (5.7) and Nonclinical Toxicology (13.2)].

1.4 Usage

Appropriate specimens for microbiological examination should be obtained in order to isolate and identify the causative pathogens and to determine their susceptibility to daptomycin.

To reduce the development of drug-resistant bacteria and maintain the effectiveness of Daptomycin for Injection and other antibacterial drugs, Daptomycin for Injection should be used only to treat or prevent infections that are proven or strongly suspected to be caused by susceptible bacteria.

When culture and susceptibility information is available, it should be considered in selecting or modifying antibacterial therapy. In the absence of such data, local epidemiology and susceptibility patterns may contribute to the empiric selection of therapy. Empiric therapy may be initiated while awaiting test results.

2 DOSAGE AND ADMINISTRATION

2.1 Important Administration Duration Instructions

Adults

Administer the appropriate volume of the reconstituted Daptomycin for Injection (concentration of 50 mg/mL) to adult patients intravenously either by injection over a two (2) minute period or by intravenous infusion over a thirty (30) minute period [see Dosage and Administration (2.2, 2.3, 2.5)].

2.2 Dosage in Adults for cSSSI

Administer Daptomycin for Injection 4 mg/kg to adult patients intravenously in 0.9% sodium chloride injection once every 24 hours for 7 to 14 days.

2.3 Dosage in Adult Patients with Staphylococcus aureus Bloodstream Infections (Bacteremia), Including Those with Right-Sided Infective Endocarditis, Caused by Methicillin-Susceptible and Methicillin-Resistant Isolates

Administer Daptomycin for Injection 6 mg/kg to adult patients intravenously in 0.9% sodium chloride injection once every 24 hours for 2 to 6 weeks. There are limited safety data for the use of daptomycin for injection for more than 28 days of therapy. In the Phase 3 trial, there were a total of 14 adult patients who were treated with daptomycin for injection for more than 28 days.

2.4 Dosage in Patients with Renal Impairment

Adult Patients:

No dosage adjustment is required in adult patients with creatinine clearance (CLCR) greater than or equal to 30 mL/min. The recommended dosage regimen for Daptomycin for Injection in adult patients with CLCR less than 30 mL/min, including adult patients on hemodialysis or continuous ambulatory peritoneal dialysis (CAPD), is 4 mg/kg (cSSSI) or 6 mg/kg (S. aureus bloodstream infections) once every 48 hours (Table 1). When possible, Daptomycin for Injection should be administered following the completion of hemodialysis on hemodialysis days [see Warnings and Precautions (5.2, 5.10), Use in Specific Populations (8.6), and Clinical Pharmacology (12.3)].

Table 1: Recommended Dosage of Daptomycin for Injection in Adult Patients
Creatinine Clearance (CLCR) | Dosage Regimen in Adults
Creatinine Clearance (CLCR) | cSSSI | S. aureus Bloodstream Infections
Greater than or equal to 30 mL/min | 4 mg/kg once every 24 hours | 6 mg/kg once every 24 hours
Less than 30 mL/min, including hemodialysis and CAPD | 4 mg/kg once every 48 hours [When possible, administer Daptomycin for Injection following the completion of hemodialysis on hemodialysis days.] | 6 mg/kg once every 48 hours

Pediatric Patients:

The dosage regimen for Daptomycin for Injection in pediatric patients with renal impairment has not been established.

2.5 Preparation and Administration of Daptomycin for Injection

There are other formulations of daptomycin that have differences concerning reconstitution and storage. Carefully follow the reconstitution and storage procedures described in this labeling.

Reconstitution of Daptomycin for Injection Vial

Daptomycin for Injection is supplied in single-dose vials, each containing 350 mg or 500 mg daptomycin as a sterile, lyophilized powder. The contents of a Daptomycin for Injection vial should be reconstituted, using aseptic technique, to 50 mg/mL as follows:

- To minimize foaming, AVOID vigorous agitation or shaking of the vial during or after reconstitution.
- Remove the polypropylene flip-off cap from the Daptomycin for Injection vial to expose the central portion of the rubber stopper. Wipe the top of the rubber stopper with an alcohol swab or other antiseptic solution and allow to dry.
- Pierce the center of the rubber stopper with the syringe needle and GENTLY inject 10 mL of 0.9% sodium chloride injection directly over the Daptomycin for Injection 500 mg drug product or 7 mL of 0.9% sodium chloride injection directly over the Daptomycin for Injection 350 mg drug product. Release the syringe plunger and allow the syringe plunger to equalize the pressure before removing the syringe from the vial.
- Hold the vial by the vial neck, tilt the vial and swirl vial contents until the product is completely reconstituted.

Administration Instructions

Parenteral drug products should be inspected visually for particulate matter prior to administration.

Slowly remove reconstituted liquid (concentration of 50 mg daptomycin/mL) from the vial using a beveled sterile needle that is 21 gauge or smaller in diameter. Administer as an intravenous injection or infusion as described below:

Adults

Intravenous Injection over a period of 2 minutes

- For intravenous (IV) injection over a period of 2 minutes in adult patients only: Administer the appropriate volume of the reconstituted Daptomycin for Injection (concentration of 50 mg/mL).

Intravenous Infusion over a period of 30 minutes

- For IV infusion over a period of 30 minutes in adult patients: The appropriate volume of the reconstituted Daptomycin for Injection (concentration of 50 mg/mL) should be further diluted, using aseptic technique, into a 50 mL IV infusion bag containing 0.9% sodium chloride injection.

No preservative or bacteriostatic agent is present in this product. Aseptic technique must be used in the preparation of final IV solution. Do not exceed the In-Use storage conditions of the reconstituted and diluted solutions of Daptomycin for Injection described below. Discard unused portions of Daptomycin for Injection.

In-Use Storage Conditions for Daptomycin for Injection Once Reconstituted in Acceptable Intravenous Diluents

Stability studies have shown that the reconstituted solution is stable in the vial for 12 hours at room temperature under normal room light and up to 48 hours if stored under refrigeration protected from light at 2°C to 8°C (36°F to 46°F).

The diluted solution is stable in the infusion bag for 12 hours under normal room light at room temperature and 48 hours (Lactated Ringer's) or 10 days (0.9% sodium chloride) if stored under refrigeration protected from light.

For Lactated Ringer's diluent, the combined storage time (reconstituted solution in vial and diluted solution in infusion bag) should not exceed 12 hours at room temperature or 48 hours under refrigeration.

For 0.9% sodium chloride diluent, the combined storage time (reconstituted solution in vial and diluted solution in infusion bag) should not exceed 12 hours at room temperature or 10 days under refrigeration.

2.6 Compatible Intravenous Solutions

Daptomycin for Injection is compatible with 0.9% sodium chloride injection for reconstitution. Reconstituted Daptomycin for Injection can be diluted with 0.9% sodium chloride injection or Lactated Ringer's injection.

2.7 Incompatibilities

Daptomycin for injection is not compatible with dextrose-containing diluents.

Daptomycin for Injection should not be used in conjunction with ReadyMED® elastomeric infusion pumps. Stability studies of daptomycin for injection solutions stored in ReadyMED® elastomeric infusion pumps identified an impurity (2-mercaptobenzothiazole) leaching from this pump system into the daptomycin for injection solution.

Because only limited data are available on the compatibility of daptomycin for injection with other IV substances, additives and other medications should not be added to Daptomycin for Injection single-dose vials or infusion bags, or infused simultaneously with Daptomycin for Injection through the same IV line. If the same IV line is used for sequential infusion of different drugs, the line should be flushed with a compatible intravenous solution before and after infusion with Daptomycin for Injection.

3 DOSAGE FORMS AND STRENGTHS

For Injection: 350 mg and 500 mg daptomycin as a sterile, pale yellow to light brown lyophilized powder for reconstitution in a single-dose vial.

4 CONTRAINDICATIONS

Daptomycin for Injection is contraindicated in patients with known hypersensitivity to daptomycin [see Warnings and Precautions (5.1)].

5 WARNINGS AND PRECAUTIONS

5.1 Anaphylaxis/Hypersensitivity Reactions

Anaphylaxis/hypersensitivity reactions have been reported with the use of antibacterial agents, including daptomycin for injection, and may be life-threatening. If an allergic reaction to Daptomycin for Injection occurs, discontinue the drug and institute appropriate therapy [see Adverse Reactions (6.2)].

5.2 Myopathy and Rhabdomyolysis

Myopathy, defined as muscle aching or muscle weakness in conjunction with increases in creatine phosphokinase (CPK) values to greater than 10 times the upper limit of normal (ULN), has been reported with the use of daptomycin for injection. Rhabdomyolysis, with or without acute renal failure, has been reported [see Adverse Reactions (6.2)].

Patients receiving Daptomycin for Injection should be monitored for the development of muscle pain or weakness, particularly of the distal extremities. In patients who receive Daptomycin for Injection, CPK levels should be monitored weekly, and more frequently in patients who received recent prior or concomitant therapy with an HMG-CoA reductase inhibitor or in whom elevations in CPK occur during treatment with Daptomycin for Injection.

In adult patients with renal impairment, both renal function and CPK should be monitored more frequently than once weekly [see Use in Specific Populations (8.6) and Clinical Pharmacology (12.3)].

In Phase 1 studies and Phase 2 clinical trials in adults, CPK elevations appeared to be more frequent when daptomycin for injection was dosed more than once daily. Therefore, Daptomycin for Injection should not be dosed more frequently than once a day.

Daptomycin for Injection should be discontinued in patients with unexplained signs and symptoms of myopathy in conjunction with CPK elevations to levels >1,000 U/L (~5× ULN), and in patients without reported symptoms who have marked elevations in CPK, with levels >2,000 U/L (≥10× ULN). In addition, consideration should be given to suspending agents associated with rhabdomyolysis, such as HMG-CoA reductase inhibitors, temporarily in patients receiving Daptomycin for Injection [see Drug Interactions (7.1)].

5.3 Eosinophilic Pneumonia

Eosinophilic pneumonia has been reported in patients receiving daptomycin for injection [see Adverse Reactions (6.2)]. In reported cases associated with daptomycin for injection, patients developed fever, dyspnea with hypoxic respiratory insufficiency, and diffuse pulmonary infiltrates or organizing pneumonia. In general, patients developed eosinophilic pneumonia 2 to 4 weeks after starting daptomycin for injection, and improved when daptomycin for injection was discontinued and steroid therapy was initiated. Recurrence of eosinophilic pneumonia upon re-exposure has been reported. Patients who develop these signs and symptoms while receiving Daptomycin for Injection should undergo prompt medical evaluation, and Daptomycin for Injection should be discontinued immediately. Treatment with systemic steroids is recommended.

5.4 Drug Reaction with Eosinophilia and Systemic Symptoms (DRESS)

DRESS has been reported in post-marketing experience with daptomycin for injection [see Adverse Reactions (6.2)]. Patients who develop skin rash, fever, peripheral eosinophilia, and systemic organ (for example, hepatic, renal, pulmonary) impairment while receiving Daptomycin for Injection should undergo medical evaluation. If DRESS is suspected, discontinue Daptomycin for Injection promptly and institute appropriate treatment.

5.5 Tubulointerstitial Nephritis (TIN)

TIN has been reported in post-marketing experience with daptomycin for injection [see Adverse Reactions (6.2)]. Patients who develop new or worsening renal impairment while receiving Daptomycin for Injection should undergo medical evaluation. If TIN is suspected, discontinue Daptomycin for Injection promptly and institute appropriate treatment.

5.6 Peripheral Neuropathy

Cases of peripheral neuropathy have been reported during the daptomycin for injection post-marketing experience [see Adverse Reactions (6.2)]. Therefore, physicians should be alert to signs and symptoms of peripheral neuropathy in patients receiving Daptomycin for Injection. Monitor for neuropathy and consider discontinuation.

5.7 Potential Nervous System and/or Muscular System Effects in Pediatric Patients Younger than 12 Months

Avoid use of Daptomycin for Injection in pediatric patients younger than 12 months due to the risk of potential effects on muscular, neuromuscular, and/or nervous systems (either peripheral and/or central) observed in neonatal dogs with intravenous daptomycin [see Nonclinical Toxicology (13.2)].

5.8 Clostridioides difficile-Associated Diarrhea

Clostridioides difficile–associated diarrhea (CDAD) has been reported with the use of nearly all systemic antibacterial agents, including daptomycin for injection, and may range in severity from mild diarrhea to fatal colitis [see Adverse Reactions (6.2)]. Treatment with antibacterial agents alters the normal flora of the colon, leading to overgrowth of C. difficile.

C. difficile produces toxins A and B, which contribute to the development of CDAD. Hypertoxin-producing strains of C. difficile cause increased morbidity and mortality, since these infections can be refractory to antimicrobial therapy and may require colectomy. CDAD must be considered in all patients who present with diarrhea following antibacterial use. Careful medical history is necessary because CDAD has been reported to occur more than 2 months after the administration of antibacterial agents.

If CDAD is suspected or confirmed, ongoing antibacterial use not directed against C. difficile may need to be discontinued. Appropriate fluid and electrolyte management, protein supplementation, antibacterial treatment of C. difficile, and surgical evaluation should be instituted as clinically indicated.

5.9 Persisting or Relapsing S. aureus Bacteremia/Endocarditis

Patients with persisting or relapsing S. aureus bacteremia/endocarditis or poor clinical response should have repeat blood cultures. If a blood culture is positive for S. aureus, minimum inhibitory concentration (MIC) susceptibility testing of the isolate should be performed using a standardized procedure, and diagnostic evaluation of the patient should be performed to rule out sequestered foci of infection. Appropriate surgical intervention (e.g., debridement, removal of prosthetic devices, valve replacement surgery) and/or consideration of a change in antibacterial regimen may be required.

Failure of treatment due to persisting or relapsing S. aureus bacteremia/endocarditis may be due to reduced daptomycin susceptibility (as evidenced by increasing MIC of the S. aureus isolate) [see Clinical Studies (14.2)].

5.10 Decreased Efficacy in Patients with Moderate Baseline Renal Impairment

Limited data are available from the two Phase 3 complicated skin and skin structure infection (cSSSI) trials regarding clinical efficacy of daptomycin for injection treatment in adult patients with creatinine clearance (CLCR) <50 mL/min; only 31/534 (6%) patients treated with daptomycin for injection in the intent-to-treat (ITT) population had a baseline CLCR <50 mL/min. Table 2 shows the number of adult patients by renal function and treatment group who were clinical successes in the Phase 3 cSSSI trials.

Table 2: Clinical Success Rates by Renal Function and Treatment Group in Phase 3 cSSSI Trials in Adult Patients (Population: ITT)
CLCR | Success Rate n/N (%)
CLCR | Daptomycin for Injection 4 mg/kg every 24h | Comparator
50–70 mL/min | 25/38 (66%) | 30/48 (63%)
30–<50 mL/min | 7/15 (47%) | 20/35 (57%)

In a subgroup analysis of the ITT population in the Phase 3 S. aureus bacteremia/endocarditis trial, clinical success rates, as determined by a treatment-blinded Adjudication Committee [see Clinical Studies (14.2)], in the daptomycin for injection-treated adult patients were lower in patients with baseline CLCR <50 mL/min (see Table 3). A decrease of the magnitude shown in Table 3 was not observed in comparator-treated patients.

Table 3: Adjudication Committee Clinical Success Rates at Test of Cure by Baseline Creatinine Clearance and Treatment Subgroup in the S. aureus Bacteremia/Endocarditis Trial in Adult Patients (Population: ITT)
Baseline CLCR | Success Rate n/N (%)
Baseline CLCR | Daptomycin for Injection 6 mg/kg every 24h |  | Comparator
Baseline CLCR | Bacteremia | Right-Sided Infective Endocarditis | Bacteremia | Right-Sided Infective Endocarditis
>80 mL/min | 30/50 (60%) | 7/14 (50%) | 19/42 (45%) | 5/11 (46%)
50–80 mL/min | 12/26 (46%) | 1/4 (25%) | 13/31 (42%) | 1/2 (50%)
30–<50 mL/min | 2/14 (14%) | 0/1 (0%) | 7/17 (41%) | 1/1 (100%)

Consider these data when selecting antibacterial therapy for use in adult patients with baseline moderate to severe renal impairment.

5.11 Increased International Normalized Ratio (INR)/Prolonged Prothrombin Time

Clinically relevant plasma concentrations of daptomycin have been observed to cause a significant concentration-dependent false prolongation of prothrombin time (PT) and elevation of International Normalized Ratio (INR) when certain recombinant thromboplastin reagents are utilized for the assay [see Drug Interactions (7.2)].

5.12 Development of Drug-Resistant Bacteria

Prescribing Daptomycin for Injection in the absence of a proven or strongly suspected bacterial infection or a prophylactic indication is unlikely to provide benefit to the patient and increases the risk of the development of drug-resistant bacteria.

6 ADVERSE REACTIONS

The following adverse reactions are described, or described in greater detail, in other sections:

- Anaphylaxis/Hypersensitivity Reactions [see Warnings and Precautions (5.1)]
- Myopathy and Rhabdomyolysis [see Warnings and Precautions (5.2)]
- Eosinophilic Pneumonia [see Warnings and Precautions (5.3)]
- Drug Reaction with Eosinophilia and Systemic Symptoms [see Warnings and Precautions (5.4)]
- Tubulointerstitial Nephritis [see Warnings and Precautions (5.5)]
- Peripheral Neuropathy [see Warnings and Precautions (5.6)]
- Increased International Normalized Ratio (INR)/Prolonged Prothrombin Time [see Warnings and Precautions (5.11) and Drug Interactions (7.2)]

6.1 Clinical Trials Experience

Because clinical trials are conducted under widely varying conditions, adverse reaction rates observed in the clinical trials of a drug cannot be directly compared with rates in the clinical trials of another drug and may not reflect the rates observed in practice.

Clinical Trial Experience in Adult Patients

Clinical trials enrolled 1,864 adult patients treated with daptomycin and 1,416 treated with comparator.

Complicated Skin and Skin Structure Infection Trials in Adults

In Phase 3 complicated skin and skin structure infection (cSSSI) trials in adult patients, daptomycin for injection was discontinued in 15/534 (2.8%) patients due to an adverse reaction, while comparator was discontinued in 17/558 (3.0%) patients.

The rates of the most common adverse reactions, organized by body system, observed in adult patients with cSSSI (receiving 4 mg/kg daptomycin) are displayed in Table 4.

Table 4: Incidence of Adverse Reactions that Occurred in ≥2% of Adult Patients in the Daptomycin for Injection Treatment Group and ≥ the Comparator Treatment Group in Phase 3 cSSSI Trials
Adverse Reaction | Adult Patients n (%)
Adverse Reaction | Daptomycin for Injection 4 mg/kg (N=534) | Comparator [Comparator: vancomycin (1 g IV every 12h) or an anti-staphylococcal semi-synthetic penicillin (i.e., nafcillin, oxacillin, cloxacillin, or flucloxacillin; 4 to 12 g/day IV in divided doses).] (N=558)
Gastrointestinal disorders
Diarrhea | 5.2 | 4.3
Nervous system disorders
Headache | 5.4 | 5.4
Dizziness | 2.2 | 2.0
Skin/subcutaneous disorders
Rash | 4.3 | 3.8
Diagnostic investigations
Abnormal liver function tests | 3.0 | 1.6
Elevated CPK | 2.8 | 1.8
Infections
Urinary tract infections | 2.4 | 0.5
Vascular disorders
Hypotension | 2.4 | 1.4
Respiratory disorders
Dyspnea | 2.1 | 1.6

Drug-related adverse reactions (possibly or probably drug-related) that occurred in <1% of adult patients receiving daptomycin in the cSSSI trials are as follows:

Body as a Whole: fatigue, weakness, rigors, flushing, hypersensitivity

Blood/Lymphatic System: leukocytosis, thrombocytopenia, thrombocytosis, eosinophilia, increased International Normalized Ratio (INR)

Cardiovascular System: supraventricular arrhythmia

Dermatologic System: eczema

Digestive System: abdominal distension, stomatitis, jaundice, increased serum lactate dehydrogenase

Metabolic/Nutritional System: hypomagnesemia, increased serum bicarbonate, electrolyte disturbance

Musculoskeletal System: myalgia, muscle cramps, muscle weakness, arthralgia

Nervous System: vertigo, mental status change, paresthesia

Special Senses: taste disturbance, eye irritation

S. aureus Bacteremia/Endocarditis Trial in Adults

In the S. aureus bacteremia/endocarditis trial involving adult patients, daptomycin for injection was discontinued in 20/120 (16.7%) patients due to an adverse reaction, while comparator was discontinued in 21/116 (18.1%) patients.

Serious Gram-negative infections (including bloodstream infections) were reported in 10/120 (8.3%) daptomycin for injection-treated patients and 0/115 comparator-treated patients. Comparator-treated patients received dual therapy that included initial gentamicin for 4 days. Infections were reported during treatment and during early and late follow-up. Gram-negative infections included cholangitis, alcoholic pancreatitis, sternal osteomyelitis/mediastinitis, bowel infarction, recurrent Crohn's disease, recurrent line sepsis, and recurrent urosepsis caused by a number of different Gram-negative bacteria.

The rates of the most common adverse reactions, organized by System Organ Class (SOC), observed in adult patients with S. aureus bacteremia/endocarditis (receiving 6 mg/kg daptomycin) are displayed in Table 5.

Table 5: Incidence of Adverse Reactions that Occurred in ≥5% of Adult Patients in the Daptomycin for Injection Treatment Group and ≥ the Comparator Treatment Group in the S. aureus Bacteremia/Endocarditis Trial
Adverse Reaction [NOS, not otherwise specified] | Adult Patients n (%)
Adverse Reaction [NOS, not otherwise specified] | Daptomycin for Injection 6 mg/kg (N=120) | Comparator [Comparator: vancomycin (1 g IV every 12h) or an anti-staphylococcal semi-synthetic penicillin (i.e., nafcillin, oxacillin, cloxacillin, or flucloxacillin; 2 g IV every 4h), each with initial low-dose gentamicin.] (N=116)
Infections and infestations
Sepsis NOS | 6 (5%) | 3 (3%)
Bacteremia | 6 (5%) | 0 (0%)
Gastrointestinal disorders
Abdominal pain NOS | 7 (6%) | 4 (3%)
General disorders and administration site conditions
Chest pain | 8 (7%) | 7 (6%)
Edema NOS | 8 (7%) | 5 (4%)
Respiratory, thoracic and mediastinal disorders
Pharyngolaryngeal pain | 10 (8%) | 2 (2%)
Skin and subcutaneous tissue disorders
Pruritus | 7 (6%) | 6 (5%)
Sweating increased | 6 (5%) | 0 (0%)
Psychiatric disorders
Insomnia | 11 (9%) | 8 (7%)
Investigations
Blood creatine phosphokinase increased | 8 (7%) | 1 (1%)
Vascular disorders
Hypertension NOS | 7 (6%) | 3 (3%)

The following reactions, not included above, were reported as possibly or probably drug-related in the daptomycin for injection-treated group:

Blood and Lymphatic System Disorders: eosinophilia, lymphadenopathy, thrombocythemia, thrombocytopenia

Cardiac Disorders: atrial fibrillation, atrial flutter, cardiac arrest

Ear and Labyrinth Disorders: tinnitus

Eye Disorders: vision blurred

Gastrointestinal Disorders: dry mouth, epigastric discomfort, gingival pain, hypoesthesia oral

Infections and Infestations: candidal infection NOS, vaginal candidiasis, fungemia, oral candidiasis, urinary tract infection fungal

Investigations: blood phosphorous increased, blood alkaline phosphatase increased, INR increased, liver function test abnormal, alanine aminotransferase increased, aspartate aminotransferase increased, prothrombin time prolonged

Metabolism and Nutrition Disorders: appetite decreased NOS

Musculoskeletal and Connective Tissue Disorders: myalgia

Nervous System Disorders: dyskinesia, paresthesia

Psychiatric Disorders: hallucination NOS

Renal and Urinary Disorders: proteinuria, renal impairment NOS

Skin and Subcutaneous Tissue Disorders: pruritus generalized, rash vesicular

Other Trials in Adults

In Phase 3 trials of community-acquired pneumonia (CAP) in adult patients, the death rate and rates of serious cardiorespiratory adverse events were higher in daptomycin for injection-treated patients than in comparator-treated patients. These differences were due to lack of therapeutic effectiveness of daptomycin for injection in the treatment of CAP in patients experiencing these adverse events [see Indications and Usage (1.3)].

Laboratory Changes in Adults

Complicated Skin and Skin Structure Infection Trials in Adults

In Phase 3 cSSSI trials of adult patients receiving daptomycin for injection at a dose of 4 mg/kg, elevations in CPK were reported as clinical adverse events in 15/534 (2.8%) daptomycin for injection-treated patients, compared with 10/558 (1.8%) comparator-treated patients. Of the 534 patients treated with daptomycin, 1 (0.2%) had symptoms of muscle pain or weakness associated with CPK elevations to greater than 4 times the upper limit of normal (ULN). The symptoms resolved within 3 days and CPK returned to normal within 7 to 10 days after treatment was discontinued [see Warnings and Precautions (5.2)]. Table 6 summarizes the CPK shifts from Baseline through End of Therapy in the cSSSI adult trials.

Table 6: Incidence of CPK Elevations from Baseline during Therapy in Either the Daptomycin for Injection Treatment Group or the Comparator Treatment Group in Phase 3 cSSSI Adult Trials
Change in CPK |  | All Adult Patients |  |  |  | Adult Patients with Normal CPK at Baseline
Change in CPK |  | Daptomycin for Injection 4 mg/kg |  | Comparator [Comparator: vancomycin (1 g IV every 12h) or an anti-staphylococcal semi-synthetic penicillin (i.e., nafcillin, oxacillin, cloxacillin, or flucloxacillin; 4 to 12 g/day IV in divided doses).] (N=459) |  | Daptomycin for Injection 4 mg/kg |  | Comparator (N=392)
Change in CPK |  | (N=430) |  | % | n | (N=374) |  | % | n
Change in CPK |  | % | n |  |  | % | n
No Increase |  | 90.7 | 390 | 91.1 | 418 | 91.2 | 341 | 91.1 | 357
Maximum Value | >1× ULN [ULN (Upper Limit of Normal) is defined as 200 U/L.] | 9.3 | 40 | 8.9 | 41 | 8.8 | 33 | 8.9 | 35
>2× ULN |  | 4.9 | 21 | 4.8 | 22 | 3.7 | 14 | 3.1 | 12
>4× ULN |  | 1.4 | 6 | 1.5 | 7 | 1.1 | 4 | 1.0 | 4
>5× ULN |  | 1.4 | 6 | 0.4 | 2 | 1.1 | 4 | 0.0 | 0
>10× ULN |  | 0.5 | 2 | 0.2 | 1 | 0.2 | 1 | 0.0 | 0
Note: Elevations in CPK observed in adult patients treated with daptomycin for injection or comparator were not clinically or statistically significantly different.

S. aureus Bacteremia/Endocarditis Trial in Adults

In the S. aureus bacteremia/endocarditis trial in adult patients, at a dose of 6 mg/kg, 11/120 (9.2%) daptomycin for injection-treated patients, including two patients with baseline CPK levels >500 U/L, had CPK elevations to levels >500 U/L, compared with 1/116 (0.9%) comparator-treated patients. Of the 11 daptomycin for injection-treated patients, 4 had prior or concomitant treatment with an HMG-CoA reductase inhibitor. Three of these 11 daptomycin for injection-treated patients discontinued therapy due to CPK elevation, while the one comparator-treated patient did not discontinue therapy [see Warnings and Precautions (5.2)].

6.2 Post-Marketing Experience

The following adverse reactions have been identified during post-approval use of daptomycin. Because these reactions are reported voluntarily from a population of uncertain size, it is not always possible to reliably estimate their frequency or establish a causal relationship to drug exposure.

Blood and lymphatic system disorders: anemia, thrombocytopenia

General and administration site conditions: pyrexia

Immune System Disorders: anaphylaxis; hypersensitivity reactions, including angioedema, pruritus, hives, shortness of breath, difficulty swallowing, truncal erythema, and pulmonary eosinophilia [see Contraindications (4) and Warnings and Precautions (5.1)]

Infections and Infestations: Clostridioides difficile–associated diarrhea [see Warnings and Precautions (5.8)]

Laboratory Investigations: platelet count decreased

Musculoskeletal Disorders: myoglobin increased; rhabdomyolysis (some reports involved patients treated concurrently with daptomycin and HMG-CoA reductase inhibitors) [see Warnings and Precautions (5.2), Drug Interactions (7.1), and Clinical Pharmacology (12.3)]

Respiratory, Thoracic, and Mediastinal Disorders: cough, eosinophilic pneumonia, organizing pneumonia [see Warnings and Precautions (5.3)]

Nervous System Disorders: peripheral neuropathy [see Warnings and Precautions (5.6)]

Skin and Subcutaneous Tissue Disorders: serious skin reactions, including drug reaction with eosinophilia and systemic symptoms (DRESS), vesiculobullous rash (with or without mucous membrane involvement, including Stevens-Johnson syndrome [SJS] and toxic epidermal necrolysis [TEN]), and acute generalized exanthematous pustulosis [see Warnings and Precautions (5.4)]

Gastrointestinal Disorders: nausea, vomiting

Metabolic and Nutritional Disorders: hyperkalemia

Renal and urinary disorders: acute kidney injury, renal insufficiency, renal failure, and tubulointerstitial nephritis (TIN) [see Warnings and Precautions (5.5)]

Special Senses: visual disturbances

7 DRUG INTERACTIONS

7.1 HMG-CoA Reductase Inhibitors

In healthy adult subjects, concomitant administration of daptomycin and simvastatin had no effect on plasma trough concentrations of simvastatin, and there were no reports of skeletal myopathy [see Clinical Pharmacology (12.3)].

However, inhibitors of HMG-CoA reductase may cause myopathy, which is manifested as muscle pain or weakness associated with elevated levels of creatine phosphokinase (CPK). In the adult Phase 3 S. aureus bacteremia/endocarditis trial, some patients who received prior or concomitant treatment with an HMG-CoA reductase inhibitor developed elevated CPK [see Adverse Reactions (6.1)]. Experience with the co-administration of HMG-CoA reductase inhibitors and daptomycin in patients is limited; therefore, consideration should be given to suspending use of HMG-CoA reductase inhibitors temporarily in patients receiving Daptomycin for Injection.

7.2 Drug-Laboratory Test Interactions

Clinically relevant plasma concentrations of daptomycin have been observed to cause a significant concentration-dependent false prolongation of prothrombin time (PT) and elevation of International Normalized Ratio (INR) when certain recombinant thromboplastin reagents are utilized for the assay. The possibility of an erroneously elevated PT/INR result due to interaction with a recombinant thromboplastin reagent may be minimized by drawing specimens for PT or INR testing near the time of trough plasma concentrations of daptomycin. However, sufficient daptomycin concentrations may be present at trough to cause interaction.

If confronted with an abnormally high PT/INR result in a patient being treated with daptomycin, it is recommended that clinicians:

1. Repeat the assessment of PT/INR, requesting that the specimen be drawn just prior to the next Daptomycin for Injection dose (i.e., at trough concentration). If the PT/INR value obtained at trough remains substantially elevated above what would otherwise be expected, consider evaluating PT/INR utilizing an alternative method.
2. Evaluate for other causes of abnormally elevated PT/INR results.

8 USE IN SPECIFIC POPULATIONS

8.1 Pregnancy

Risk Summary

Limited published data on use of daptomycin in pregnant women are insufficient to inform a drug-associated risk for major birth defects and miscarriage. In animal reproduction studies performed in rats and rabbits daptomycin was administered intravenously during organogenesis at doses 2 and 4-times, respectively, the recommended 6 mg/kg human dose (on a body surface area basis). No evidence of adverse developmental outcomes was observed.

The background risk of major birth defects and miscarriage for the indicated population is unknown. All pregnancies have a background risk of birth defect, loss, or other adverse outcomes. In the U.S. general population, the estimated background risk of major birth defects and miscarriage in clinically recognized pregnancies is 2–4% and 15–20%, respectively.

Data

Animal Data

In pregnant rats, daptomycin was administered intravenously at doses of 5, 20, or 75 mg/kg/day during the gestation days 6 to 18. Maternal body weight gain was decreased at 75 mg/kg/day. No embryo/fetal effects were noted at the highest dose of 75 mg/kg/day, a dose approximately 2-fold higher than in humans at the recommended maximum dose of 6 mg/kg (based on body surface area).

In pregnant rabbits, daptomycin was administered intravenously at doses of 5, 20, or 75 mg/kg/day during the gestation days 6 to 15. Maternal body weight gain and food consumption were decreased at 75 mg/kg/day. No embryo/fetal effects were noted at the highest dose of 75 mg/kg/day, a dose approximately 4-fold higher than in humans at the maximum recommended dose of 6mg/kg (based on body surface area).

In a combined fertility and pre/postnatal development study, daptomycin was administered intravenously to female rats at doses of 2, 25, 75 mg/kg/day from 14 days pre-mating through lactation/postpartum day 20). No effects on pre/postnatal development were observed up to the highest dose of 75 mg/kg/day, a dose approximately 2-fold higher than the maximum recommended human dose of 6 mg/kg (based on body surface area)^1.

8.2 Lactation

Risk Summary

Limited published data report that daptomycin is present in human milk at infant doses of 0.1% of the maternal dose (see Data)^2,3,4. There is no information on the effects of daptomycin on the breastfed infant or the effects of daptomycin on milk production. The developmental and health benefits of breastfeeding should be considered along with the mother's clinical need for Daptomycin for Injection and any potential adverse effects on the breastfed infant from Daptomycin for Injection or from the underlying maternal condition.

8.4 Pediatric Use

This Daptomycin for Injection product is not approved for use in pediatric patients.

Safety and effectiveness of daptomycin for injection in pediatric patients below the age of one year have not been established. Avoid use of Daptomycin for Injection in pediatric patients younger than one year of age due to the risk of potential effects on muscular, neuromuscular, and/or nervous systems (either peripheral and/or central) observed in neonatal dogs [see Warnings and Precautions (5.7) and Nonclinical Toxicology (13.2)].

Daptomycin for Injection is not indicated in pediatric patients with renal impairment because dosage has not been established in these patients.

8.5 Geriatric Use

Of the 534 adult patients treated with daptomycin for injection in Phase 3 controlled clinical trials of complicated skin and skin structure infections (cSSSI), 27% were 65 years of age or older and 12% were 75 years of age or older. Of the 120 adult patients treated with daptomycin for injection in the Phase 3 controlled clinical trial of S. aureus bacteremia/endocarditis, 25% were 65 years of age or older and 16% were 75 years of age or older. In Phase 3 adult clinical trials of cSSSI and S. aureus bacteremia/endocarditis, clinical success rates were lower in patients ≥65 years of age than in patients <65 years of age. In addition, treatment-emergent adverse events were more common in patients ≥65 years of age than in patients <65 years of age.

The exposure of daptomycin was higher in healthy elderly subjects than in healthy young adult subjects. However, no adjustment of Daptomycin for Injection dosage is warranted for elderly patients with creatinine clearance (CLCR) ≥30 mL/min [see Dosage and Administration (2.4) and Clinical Pharmacology (12.3)].

8.6 Patients with Renal Impairment

Daptomycin is eliminated primarily by the kidneys; therefore, a modification of daptomycin dosage interval is recommended for adult patients with CLCR <30 mL/min, including patients receiving hemodialysis or continuous ambulatory peritoneal dialysis (CAPD). In adult patients with renal impairment, both renal function and creatine phosphokinase (CPK) should be monitored more frequently than once weekly [see Dosage and Administration (2.4), Warnings and Precautions (5.2, 5.10), and Clinical Pharmacology (12.3)].

The dosage regimen for Daptomycin for Injection in pediatric patients with renal impairment has not been established.

10 OVERDOSAGE

In the event of overdosage, supportive care is advised with maintenance of glomerular filtration. Daptomycin is cleared slowly from the body by hemodialysis (approximately 15% of the administered dose is removed over 4 hours) and by peritoneal dialysis (approximately 11% of the administered dose is removed over 48 hours). The use of high-flux dialysis membranes during 4 hours of hemodialysis may increase the percentage of dose removed compared with that removed by low-flux membranes.

11 DESCRIPTION

Daptomycin for Injection contains daptomycin, a cyclic lipopeptide antibacterial agent derived from the fermentation of Streptomyces roseosporus. The chemical name is N-decanoyl-L-tryptophyl-D-asparaginyl-L-aspartyl-L‑threonylglycyl-L-ornithyl-L-aspartyl-D-alanyl-L-aspartylglycyl-D-seryl-threo-3-methyl-L-glutamyl-3-anthraniloyl-L-alanine ε1‑ lactone. The chemical structure is:

The empirical formula is C72H101N17O26; the molecular weight is 1620.67. Daptomycin for Injection is supplied in a single-dose vial as a sterile, preservative-free, pale yellow to light brown, lyophilized cake containing 350 mg or 500 mg of daptomycin for intravenous (IV) use following reconstitution with 0.9% sodium chloride injection [see Dosage and Administration (2.5)]. Daptomycin for Injection 350 mg per vial, contains 350 mg daptomycin and 53.8 mg citric acid. Sodium hydroxide is used to adjust the pH. Daptomycin for Injection 500 mg per vial contains 500 mg daptomycin, and 76.8 mg citric acid. Sodium hydroxide is used to adjust the pH. Freshly reconstituted solutions of Daptomycin for Injection range in color from light yellow to light brown.

12 CLINICAL PHARMACOLOGY

12.1 Mechanism of Action

Daptomycin is an antibacterial drug [see Clinical Pharmacology (12.4)].

12.2 Pharmacodynamics

Based on animal models of infection, the antimicrobial activity of daptomycin appears to correlate with the AUC/MIC (area under the concentration-time curve/minimum inhibitory concentration) ratio for certain pathogens, including S. aureus. The principal pharmacokinetic/pharmacodynamic parameter best associated with clinical and microbiological cure has not been elucidated in clinical trials with daptomycin for injection.

12.3 Pharmacokinetics

Daptomycin for Injection Administered over a 30-Minute Period in Adults

The mean and standard deviation (SD) pharmacokinetic parameters of daptomycin at steady-state following intravenous (IV) administration of daptomycin for injection over a 30-minute period at 4 to 12 mg/kg every 24h to healthy young adults are summarized in Table 7.

Table 7: Mean (SD) Daptomycin Pharmacokinetic Parameters in Healthy Adult Volunteers at Steady-State
Dose [Daptomycin for injection was administered by IV infusion over a 30-minute period.] [Doses of daptomycin for injection in excess of 6 mg/kg have not been approved.] (mg/kg) | Pharmacokinetic Parameters [AUC0–24, area under the concentration-time curve from 0 to 24 hours; t1/2, elimination half-life; Vss, volume of distribution at steady-state; CLT, total plasma clearance; Cmax, maximum plasma concentration.]
Dose [Daptomycin for injection was administered by IV infusion over a 30-minute period.] [Doses of daptomycin for injection in excess of 6 mg/kg have not been approved.] (mg/kg) | AUC0–24 (mcg∙h/mL) | t1/2 (h) | Vss (L/kg) | CLT (mL/h/kg) | Cmax (mcg/mL)
4 (N=6) | 494 (75) | 8.1 (1.0) | 0.096 (0.009) | 8.3 (1.3) | 57.8 (3.0)
6 (N=6) | 632 (78) | 7.9 (1.0) | 0.101 (0.007) | 9.1 (1.5) | 93.9 (6.0)
8 (N=6) | 858 (213) | 8.3 (2.2) | 0.101 (0.013) | 9.0 (3.0) | 123.3 (16.0)
10 (N=9) | 1039 (178) | 7.9 (0.6) | 0.098 (0.017) | 8.8 (2.2) | 141.1 (24.0)
12 (N=9) | 1277 (253) | 7.7 (1.1) | 0.097 (0.018) | 9.0 (2.8) | 183.7 (25.0)

Daptomycin pharmacokinetics were generally linear and time-independent at Daptomycin for Injection doses of 4 to 12 mg/kg every 24h administered by IV infusion over a 30-minute period for up to 14 days. Steady-state trough concentrations were achieved by the third daily dose. The mean (SD) steady-state trough concentrations attained following the administration of 4, 6, 8, 10, and 12 mg/kg every 24h were 5.9 (1.6), 6.7 (1.6), 10.3 (5.5), 12.9 (2.9), and 13.7 (5.2) mcg/mL, respectively.

Daptomycin for Injection Administered over a 2-Minute Period in Adults

Following IV administration of daptomycin for injection over a 2-minute period to healthy adult volunteers at doses of 4 mg/kg (N=8) and 6 mg/kg (N=12), the mean (SD) steady-state systemic exposure (AUC) values were 475 (71) and 701 (82) mcg∙h/mL, respectively. Values for maximum plasma concentration (Cmax) at the end of the 2-minute period could not be determined adequately in this study. However, using pharmacokinetic parameters from 14 healthy adult volunteers who received a single-dose of daptomycin for injection 6 mg/kg IV administered over a 30-minute period in a separate study, steady-state Cmax values were simulated for daptomycin for injection 4 and 6 mg/kg IV administered over a 2-minute period. The simulated mean (SD) steady-state Cmax values were 77.7 (8.1) and 116.6 (12.2) mcg/mL, respectively.

Distribution

Daptomycin is reversibly bound to human plasma proteins, primarily to serum albumin, in a concentration-independent manner. The overall mean binding ranges from 90 to 93%.

In clinical studies, mean serum protein binding in adult subjects with creatinine clearance (CLCR) ≥30 mL/min was comparable to that observed in healthy adult subjects with normal renal function. However, there was a trend toward decreasing serum protein binding among subjects with CLCR <30 mL/min (88%), including those receiving hemodialysis (86%) and continuous ambulatory peritoneal dialysis (CAPD) (84%). The protein binding of daptomycin in adult subjects with moderate hepatic impairment (Child-Pugh Class B) was similar to that in healthy adult subjects.

The volume of distribution at steady-state (Vss) of daptomycin in healthy adult subjects was approximately 0.1 L/kg and was independent of dose.

Metabolism

In in vitro studies, daptomycin was not metabolized by human liver microsomes.

In 5 healthy adults after infusion of radiolabeled ^14C-daptomycin, the plasma total radioactivity was similar to the concentration determined by microbiological assay. Inactive metabolites were detected in urine, as determined by the difference between total radioactive concentrations and microbiologically active concentrations. In a separate study, no metabolites were observed in plasma on Day 1 following the administration of daptomycin for injection at 6 mg/kg to adult subjects. Minor amounts of three oxidative metabolites and one unidentified compound were detected in urine. The site of metabolism has not been identified.

Excretion

Daptomycin is excreted primarily by the kidneys. In a mass balance study of 5 healthy adult subjects using radiolabeled daptomycin, approximately 78% of the administered dose was recovered from urine based on total radioactivity (approximately 52% of the dose based on microbiologically active concentrations), and 5.7% of the administered dose was recovered from feces (collected for up to 9 days) based on total radioactivity.

Specific Populations

Patients with Renal Impairment

Population-derived pharmacokinetic parameters were determined for infected adult patients (complicated skin and skin structure infections [cSSSI] and S. aureus bacteremia) and noninfected adult subjects with various degrees of renal function (Table 8). Total plasma clearance (CLT), elimination half-life (t1/2), and volume of distribution at steady-state (Vss) in patients with cSSSI were similar to those in patients with S. aureus bacteremia. Following administration of daptomycin for injection 4 mg/kg every 24h by IV infusion over a 30-minute period, the mean CLT was 9%, 22%, and 46% lower among subjects and patients with mild (CLCR 50–80 mL/min), moderate (CLCR 30–<50 mL/min), and severe (CLCR <30 mL/min) renal impairment, respectively, than in those with normal renal function (CLCR >80 mL/min). The mean steady-state systemic exposure (AUC), t1/2, and Vss increased with decreasing renal function, although the mean AUC for patients with CLCR 30–80 mL/min was not markedly different from the mean AUC for patients with normal renal function. The mean AUC for patients with CLCR <30 mL/min and for patients on dialysis (CAPD and hemodialysis dosed post-dialysis) was approximately 2 and 3 times higher, respectively, than for patients with normal renal function. The mean Cmax ranged from 60 to 70 mcg/mL in patients with CLCR ≥30 mL/min, while the mean Cmax for patients with CLCR <30 mL/min ranged from 41 to 58 mcg/mL. After administration of daptomycin for injection 6 mg/kg every 24h by IV infusion over a 30-minute period, the mean Cmax ranged from 80 to 114 mcg/mL in patients with mild to moderate renal impairment and was similar to that of patients with normal renal function.

Table 8: Mean (SD) Daptomycin Population Pharmacokinetic Parameters Following Infusion of Daptomycin for Injection 4 mg/kg or 6 mg/kg to Infected Adult Patients and Noninfected Adult Subjects with Various Degrees of Renal Function
Renal Function | Pharmacokinetic Parameters [CLCR, creatinine clearance estimated using the Cockcroft-Gault equation with actual body weight; CAPD, continuous ambulatory peritoneal dialysis; AUC0–∞, area under the concentration-time curve extrapolated to infinity; AUCSS, area under the concentration-time curve calculated over the 24-hour dosing interval at steady-state; Cmin, SS, trough concentration at steady-state; NA, not applicable.]
Renal Function | t1/2 [Parameters obtained following a single dose from patients with complicated skin and skin structure infections and healthy subjects.] (h) 4 mg/kg | Vss (L/kg) 4 mg/kg | CLT (mL/h/kg) 4 mg/kg | AUC0–∞ (mcg∙h/mL) 4 mg/kg | AUCss [Parameters obtained at steady-state from patients with S. aureus bacteremia.] (mcg∙h/mL) 6 mg/kg | Cmin, SS (mcg/mL) 6 mg/kg
Normal (CLCR >80 mL/min) | 9.39 (4.74) N=165 | 0.13 (0.05) N=165 | 10.9 (4.0) N=165 | 417 (155) N=165 | 545 (296) N=62 | 6.9 (3.5) N=61
Mild Renal Impairment (CLCR 50–80 mL/min) | 10.75 (8.36) N=64 | 0.12 (0.05) N=64 | 9.9 (4.0) N=64 | 466 (177) N=64 | 637 (215) N=29 | 12.4 (5.6) N=29
Moderate Renal Impairment (CLCR 30–<50 mL/min) | 14.70 (10.50) N=24 | 0.15 (0.06) N=24 | 8.5 (3.4) N=24 | 560 (258) N=24 | 868 (349) N=15 | 19.0 (9.0) N=14
Severe Renal Impairment (CLCR <30 mL/min) | 27.83(14.85) N=8 | 0.20 (0.15) N=8 | 5.9 (3.9) N=8 | 925 (467) N=8 | 1050 (892) N=2 | 24.4 (21.4) N=2
Hemodialysis | 30.51 (6.51) N=16 | 0.16 (0.04) N=16 | 3.9 (2.1) N=16 | 1193 (399) N=16 | NA | NA
CAPD | 27.56 (4.53) N=5 | 0.11 (0.02) N=5 | 2.9 (0.4) N=5 | 1409 (238) N=5 | NA | NA
Note: Daptomycin for injection was administered over a 30-minute period.

Because renal excretion is the primary route of elimination, adjustment of daptomycin for injection dosage interval is necessary in adult patients with severe renal impairment (CLCR <30 mL/min) [see Dosage and Administration (2.6)].

Patients with Hepatic Impairment

The pharmacokinetics of daptomycin were evaluated in 10 adult subjects with moderate hepatic impairment (Child-Pugh Class B) and compared with those in healthy adult volunteers (N=9) matched for gender, age, and weight. The pharmacokinetics of daptomycin were not altered in subjects with moderate hepatic impairment. No dosage adjustment is warranted when daptomycin for injection is administered to patients with mild to moderate hepatic impairment. The pharmacokinetics of daptomycin in patients with severe hepatic impairment (Child-Pugh Class C) have not been evaluated.

Gender

No clinically significant gender-related differences in daptomycin pharmacokinetics have been observed. No dosage adjustment is warranted based on gender when daptomycin for injection is administered.

Geriatric Patients

The pharmacokinetics of daptomycin were evaluated in 12 healthy elderly subjects (≥75 years of age) and 11 healthy young adult controls (18 to 30 years of age). Following administration of a single 4 mg/kg dose of daptomycin for injection by IV infusion over a 30-minute period, the mean total clearance of daptomycin was approximately 35% lower and the mean AUC0–∞ was approximately 58% higher in elderly subjects than in healthy young adult subjects. There were no differences in Cmax [see Use in Specific Populations (8.5)].

Obese Patients

The pharmacokinetics of daptomycin were evaluated in 6 moderately obese (Body Mass Index [BMI] 25 to 39.9 kg/m^2) and 6 extremely obese (BMI ≥40 kg/m^2) adult subjects and controls matched for age, gender, and renal function. Following administration of daptomycin for injection by IV infusion over a 30-minute period as a single 4 mg/kg dose based on total body weight, the total plasma clearance of daptomycin normalized to total body weight was approximately 15% lower in moderately obese subjects and 23% lower in extremely obese subjects than in nonobese controls. The AUC0–∞ of daptomycin was approximately 30% higher in moderately obese subjects and 31% higher in extremely obese subjects than in nonobese controls. The differences were most likely due to differences in the renal clearance of daptomycin. No adjustment of Daptomycin for Injection dosage is warranted in obese patients.

Drug Interaction Studies

In Vitro Studies

In vitro studies with human hepatocytes indicate that daptomycin does not inhibit or induce the activities of the following human cytochrome P450 isoforms: 1A2, 2A6, 2C9, 2C19, 2D6, 2E1, and 3A4. It is unlikely that daptomycin will inhibit or induce the metabolism of drugs metabolized by the P450 system.

Aztreonam

In a study in which 15 healthy adult subjects received a single dose of daptomycin for injection 6 mg/kg IV and a combination dose of daptomycin 6 mg/kg IV and aztreonam 1 g IV, administered over a 30-minute period, the Cmax and AUC0–∞ of daptomycin were not significantly altered by aztreonam.

Tobramycin

In a study in which 6 healthy adult males received a single dose of daptomycin for injection 2 mg/kg IV, tobramycin 1 mg/kg IV, and both in combination, administered over a 30-minute period, the mean Cmax and AUC0–∞ of daptomycin were 12.7% and 8.7% higher, respectively, when daptomycin for injection was co-administered with tobramycin. The mean Cmax and AUC0–∞ of tobramycin were 10.7% and 6.6% lower, respectively, when tobramycin was co-administered with daptomycin for injection. These differences were not statistically significant. The interaction between daptomycin and tobramycin with a clinical dose of daptomycin for injection is unknown.

Warfarin

In 16 healthy adult subjects, administration of daptomycin for injection 6 mg/kg every 24h by IV infusion over a 30-minute period for 5 days, with co-administration of a single oral dose of warfarin (25 mg) on the 5th day, had no significant effect on the pharmacokinetics of either drug and did not significantly alter the INR (International Normalized Ratio).

Simvastatin

In 20 healthy adult subjects on a stable daily dose of simvastatin 40 mg, administration of daptomycin for injection 4 mg/kg every 24h by IV infusion over a 30-minute period for 14 days (N=10) had no effect on plasma trough concentrations of simvastatin and was not associated with a higher incidence of adverse events, including skeletal myopathy, than in subjects receiving placebo once daily (N=10) [see Warnings and Precautions (5.2) and Drug Interactions (7.1)].

Probenecid

Concomitant administration of probenecid (500 mg 4 times daily) and a single dose of daptomycin for injection 4 mg/kg by IV infusion over a 30-minute period in adults did not significantly alter the Cmax or AUC0–∞ of daptomycin.

12.4 Microbiology

Daptomycin belongs to the cyclic lipopeptide class of antibacterials. Daptomycin has clinical utility in the treatment of infections caused by aerobic, Gram-positive bacteria. The in vitro spectrum of activity of daptomycin encompasses most clinically relevant Gram-positive pathogenic bacteria.

Daptomycin exhibits rapid, concentration-dependent bactericidal activity against Gram-positive bacteria in vitro. This has been demonstrated both by time-kill curves and by MBC/MIC (minimum bactericidal concentration/minimum inhibitory concentration) ratios using broth dilution methodology. Daptomycin maintained bactericidal activity in vitro against stationary phase S. aureus in simulated endocardial vegetations. The clinical significance of this is not known.

Mechanism of Action

Daptomycin binds to bacterial cell membranes and causes a rapid depolarization of membrane potential. This loss of membrane potential causes inhibition of DNA, RNA, and protein synthesis, which results in bacterial cell death.

Resistance

The mechanism(s) of daptomycin resistance is not fully understood. Currently, there are no known transferable elements that confer resistance to daptomycin.

Interactions with Other Antibacterials

In vitro studies have investigated daptomycin interactions with other antibacterials. Antagonism, as determined by kill curve studies, has not been observed. In vitro synergistic interactions of daptomycin with aminoglycosides, β-lactam antibacterials, and rifampin have been shown against some isolates of staphylococci (including some methicillin-resistant isolates) and enterococci (including some vancomycin-resistant isolates).

Complicated Skin and Skin Structure Infection (cSSSI) Trials in Adults

The emergence of daptomycin non-susceptible isolates occurred in 2 infected patients across the set of Phase 2 and pivotal Phase 3 clinical trials of cSSSI in adult patients. In one case, a non-susceptible S. aureus was isolated from a patient in a Phase 2 trial who received daptomycin for injection at less than the protocol-specified dose for the initial 5 days of therapy. In the second case, a non-susceptible Enterococcus faecalis was isolated from a patient with an infected chronic decubitus ulcer who was enrolled in a salvage trial.

S. aureus Bacteremia/Endocarditis and Other Post-Approval Trials in Adults

In subsequent clinical trials in adult patients, non-susceptible isolates were recovered. S. aureus was isolated from a patient in a compassionate-use trial and from 7 patients in the S. aureus bacteremia/endocarditis trial [see Clinical Studies (14.2)]. An E. faecium was isolated from a patient in a vancomycin-resistant enterococci trial.

Antimicrobial Activity

Daptomycin has been shown to be active against most isolates of the following microorganisms both in vitro and in clinical infections [see Indications and Usage (1)].

Gram-Positive Bacteria

Enterococcus faecalis (vancomycin-susceptible isolates only)
Staphylococcus aureus (including methicillin-resistant isolates)
Streptococcus agalactiae
Streptococcus dysgalactiae subsp. equisimilis
Streptococcus pyogenes

The following in vitro data are available, but their clinical significance is unknown. At least 90 percent of the following bacteria exhibit an in vitro minimum inhibitory concentration (MIC) less than or equal to the susceptible breakpoint for daptomycin against isolates of similar genus or organism group. However, the efficacy of daptomycin in treating clinical infections caused by these bacteria has not been established in adequate and well-controlled clinical trials.

Gram-Positive Bacteria

Corynebacterium jeikeium
Enterococcus faecalis (vancomycin-resistant isolates)
Enterococcus faecium (including vancomycin-resistant isolates)
Staphylococcus epidermidis (including methicillin-resistant isolates) Staphylococcus haemolyticus

Susceptibility Testing

For specific information regarding susceptibility test interpretive criteria, and associated test methods and quality control standards recognized by FDA for daptomycin, please see: https://www.fda.gov/STIC.

13 NONCLINICAL TOXICOLOGY

13.1 Carcinogenesis, Mutagenesis, Impairment of Fertility

Long-term carcinogenicity studies in animals have not been conducted to evaluate the carcinogenic potential of daptomycin for injection. However, neither mutagenic nor clastogenic potential was found in a battery of genotoxicity tests, including the Ames assay, a mammalian cell gene mutation assay, a test for chromosomal aberrations in Chinese hamster ovary cells, an in vivo micronucleus assay, an in vitro DNA repair assay, and an in vivo sister chromatid exchange assay in Chinese hamsters.

Daptomycin did not affect the fertility or reproductive performance of male and female rats when administered intravenously at doses of 25, 75, or 150 mg/kg/day, which is approximately up to 9 times the estimated human exposure level based upon AUCs (or approximately up to 4 times the recommended human dose of 6 mg/kg based on body surface area comparison).

13.2 Animal Toxicology and/or Pharmacology

Adult Animals

In animals, daptomycin administration has been associated with effects on skeletal muscle. However, there were no changes in cardiac or smooth muscle. Skeletal muscle effects were characterized by microscopic degenerative/regenerative changes and variable elevations in creatine phosphokinase (CPK). No fibrosis or rhabdomyolysis was evident in repeat-dose studies up to the highest doses tested in rats (150 mg/kg/day) and dogs (100 mg/kg/day). The degree of skeletal myopathy showed no increase when treatment was extended from 1 month to up to 6 months. Severity was dose-dependent. All muscle effects, including microscopic changes, were fully reversible within 30 days following the cessation of dosing.

In adult animals, effects on peripheral nerve (characterized by axonal degeneration and frequently accompanied by significant losses of patellar reflex, gag reflex, and pain perception) were observed at daptomycin doses higher than those associated with skeletal myopathy. Deficits in the dogs' patellar reflexes were seen within 2 weeks after the start of treatment at 40 mg/kg/day (9 times the human Cmax at the 6 mg/kg/day dose), with some clinical improvement noted within 2 weeks after the cessation of dosing. However, at 75 mg/kg/day for 1 month, 7 of 8 dogs failed to regain full patellar reflex responses within a 3-month recovery period. In a separate study in dogs receiving doses of 75 and 100 mg/kg/day for 2 weeks, minimal residual histological changes were noted at 6 months after the cessation of dosing. However, recovery of peripheral nerve function was evident.

Tissue distribution studies in rats showed that daptomycin is retained in the kidney but appears to penetrate the blood-brain barrier only minimally following single and multiple doses.

Juvenile Animals

Target organs of daptomycin-related effects in 7-week-old juvenile dogs were skeletal muscle and nerve, the same target organs as in adult dogs. In juvenile dogs, nerve effects were noted at lower daptomycin blood concentrations than in adult dogs following 28 days of dosing. In contrast to adult dogs, juvenile dogs also showed evidence of effects in nerves of the spinal cord as well as peripheral nerves after 28 days of dosing. No nerve effects were noted in juvenile dogs following 14 days of dosing at doses up to 75 mg/kg/day.

Administration of daptomycin to 7-week-old juvenile dogs for 28 days at doses of 50 mg/kg/day produced minimal degenerative effects on the peripheral nerve and spinal cord in several animals, with no corresponding clinical signs. A dose of 150 mg/kg/day for 28 days produced minimal degeneration in the peripheral nerve and spinal cord as well as minimal to mild degeneration of the skeletal muscle in a majority of animals, accompanied by slight to severe muscle weakness evident in most dogs. Following a 28-day recovery phase, microscopic examination revealed recovery of the skeletal muscle and the ulnar nerve effects, but nerve degeneration in the sciatic nerve and spinal cord was still observed in all 150 mg/kg/day dogs.

Following once-daily administration of daptomycin to juvenile dogs for 28 days, microscopic effects in nerve tissue were noted at a Cmax value of 417 mcg/mL, which is approximately 3-fold less than the Cmax value associated with nerve effects in adult dogs treated once daily with daptomycin for 28 days (1,308 mcg/mL).

Neonatal Animals

Neonatal dogs (4 to 31 days old) were more sensitive to daptomycin-related adverse nervous system and/or muscular system effects than either juvenile or adult dogs. In neonatal dogs, adverse nervous system and/or muscular system effects were associated with a Cmax value approximately 3-fold less than the Cmax in juvenile dogs, and 9-fold less than the Cmax in adult dogs following 28 days of dosing. At a dose of 25 mg/kg/day with associated Cmax and AUCinf values of 147 mcg/mL and 717 mcg∙h/mL, respectively (1.6 and 1.0-fold the adult human Cmax and AUC, respectively, at the 6 mg/kg/day dose), mild clinical signs of twitching and one incidence of muscle rigidity were observed with no corresponding effect on body weight. These effects were found to be reversible within 28 days after treatment had stopped.

At higher dose levels of 50 and 75 mg/kg/day with associated Cmax and AUCinf values of ≥321 mcg/mL and ≥1,470 mcg∙h/mL, respectively, marked clinical signs of twitching, muscle rigidity in the limbs, and impaired use of limbs were observed. Resulting decreases in body weights and overall body condition at doses ≥50 mg/kg/day necessitated early discontinuation by postnatal day (PND) 19.

Histopathological assessment did not reveal any daptomycin-related changes in the peripheral and central nervous system tissue, as well as in the skeletal muscle or other tissues assessed, at any dose level.

No adverse effects were observed in the dogs that received daptomycin at 10 mg/kg/day, the NOAEL, with associated Cmax and AUCinf values of 62 mcg/mL and 247 mcg∙h/mL, respectively (or 0.6 and 0.4-fold the adult human Cmax and AUC, respectively at the 6 mg/kg dose).

14 CLINICAL STUDIES

14.1 Complicated Skin and Skin Structure Infections

Adults with cSSSI

Adult patients with clinically documented complicated skin and skin structure infections (cSSSI) (Table 9) were enrolled in two randomized, multinational, multi-center, investigator-blinded trials comparing daptomycin for injection (4 mg/kg IV every 24h) with either vancomycin (1 g IV every 12h) or an anti-staphylococcal semi-synthetic penicillin (i.e., nafcillin, oxacillin, cloxacillin, or flucloxacillin; 4 to 12 g IV per day). Patients could switch to oral therapy after a minimum of 4 days of IV treatment if clinical improvement was demonstrated. Patients known to have bacteremia at baseline were excluded. Patients with creatinine clearance (CLCR) between 30 and 70 mL/min were to receive a lower dose of daptomycin for injection as specified in the protocol; however, the majority of patients in this subpopulation did not have the dose of daptomycin for injection adjusted.

Table 9: Investigator's Primary Diagnosis in the cSSSI Trials in Adult Patients (Population: ITT)
Primary Diagnosis | Adult Patients (Daptomycin for Injection/ Comparator [Comparator: vancomycin (1 g IV every 12h) or an anti-staphylococcal semi-synthetic penicillin (i.e., nafcillin, oxacillin, cloxacillin, or flucloxacillin; 4 to 12 g/day IV in divided doses).])
Primary Diagnosis | Study 9801 N=264/N=266 | Study 9901 N=270/N=292 | Pooled N=534/N=558
Wound Infection | 99 (38%)/116 (44%) | 102 (38%)/108 (37%) | 201 (38%)/224 (40%)
Major Abscess | 55 (21%)/43 (16%) | 59 (22%)/65 (22%) | 114 (21%)/108 (19%)
Ulcer Infection | 71 (27%)/75 (28%) | 53 (20%)/68 (23%) | 124 (23%)/143 (26%)
Other Infection [The majority of cases were subsequently categorized as complicated cellulitis, major abscesses, or traumatic wound infections.] | 39 (15%)/32 (12%) | 56 (21%)/51 (18%) | 95 (18%)/83 (15%)

One trial was conducted primarily in the United States and South Africa (study 9801), and the second was conducted at non-US sites only (study 9901). The two trials were similar in design but differed in patient characteristics, including history of diabetes and peripheral vascular disease. There were a total of 534 adult patients treated with daptomycin for injection and 558 treated with comparator in the two trials. The majority (89.7%) of patients received IV medication exclusively.

The efficacy endpoints in both trials were the clinical success rates in the intent-to-treat (ITT) population and in the clinically evaluable (CE) population. In study 9801, clinical success rates in the ITT population were 62.5% (165/264) in patients treated with daptomycin for injection and 60.9% (162/266) in patients treated with comparator drugs. Clinical success rates in the CE population were 76.0% (158/208) in patients treated with daptomycin for injection and 76.7% (158/206) in patients treated with comparator drugs. In study 9901, clinical success rates in the ITT population were 80.4% (217/270) in patients treated with daptomycin for injection and 80.5% (235/292) in patients treated with comparator drugs. Clinical success rates in the CE population were 89.9% (214/238) in patients treated with daptomycin for injection and 90.4% (226/250) in patients treated with comparator drugs.

The success rates by pathogen for microbiologically evaluable patients are presented in Table 10.

Table 10: Clinical Success Rates by Infecting Pathogen in the cSSSI Trials in Adult Patients (Population: Microbiologically Evaluable)
Pathogen | Success Rate n/N (%)
Pathogen | Daptomycin for Injection | Comparator [Comparator: vancomycin (1 g IV every 12h) or an anti-staphylococcal semi-synthetic penicillin (i.e., nafcillin, oxacillin, cloxacillin, or flucloxacillin; 4 to 12 g/day IV in divided doses).]
Methicillin-susceptible Staphylococcus aureus (MSSA) [As determined by the central laboratory.] | 170/198 (86%) | 180/207 (87%)
Methicillin-resistant Staphylococcus aureus (MRSA) | 21/28 (75%) | 25/36 (69%)
Streptococcus pyogenes | 79/84 (94%) | 80/88 (91%)
Streptococcus agalactiae | 23/27 (85%) | 22/29 (76%)
Streptococcus dysgalactiae subsp. equisimilis | 8/8 (100%) | 9/11 (82%)
Enterococcus faecalis (vancomycin-susceptible only) | 27/37 (73%) | 40/53 (76%)

14.2 S. aureus Bacteremia/Endocarditis

Adults with S. aureus Bacteremia/Endocarditis

The efficacy of daptomycin for injection in the treatment of adult patients with S. aureus bacteremia was demonstrated in a randomized, controlled, multinational, multi-center, open-label trial. In this trial, adult patients with at least one positive blood culture for S. aureus obtained within 2 calendar days prior to the first dose of study drug and irrespective of source were enrolled and randomized to either daptomycin for injection (6 mg/kg IV every 24h) or standard of care [an anti-staphylococcal semi-synthetic penicillin 2 g IV every 4h (nafcillin, oxacillin, cloxacillin, or flucloxacillin) or vancomycin 1 g IV every 12h, each with initial gentamicin 1 mg/kg IV every 8 hours for first 4 days]. Of the patients in the comparator group, 93% received initial gentamicin for a median of 4 days, compared with 1 patient (<1%) in the daptomycin for injection group. Patients with prosthetic heart valves, intravascular foreign material that was not planned for removal within 4 days after the first dose of study medication, severe neutropenia, known osteomyelitis, polymicrobial bloodstream infections, creatinine clearance <30 mL/min, and pneumonia were excluded.

Upon entry, patients were classified for likelihood of endocarditis using the modified Duke criteria (Possible, Definite, or Not Endocarditis). Echocardiography, including a transesophageal echocardiogram (TEE), was performed within 5 days following study enrollment. The choice of comparator agent was based on the oxacillin susceptibility of the S. aureus isolate. The duration of study treatment was based on the investigator's clinical diagnosis. Final diagnoses and outcome assessments at Test of Cure (6 weeks after the last treatment dose) were made by a treatment-blinded Adjudication Committee, using protocol-specified clinical definitions and a composite primary efficacy endpoint (clinical and microbiological success) at the Test of Cure visit.

A total of 246 patients ≥18 years of age (124 daptomycin for injection, 122 comparator) with S. aureus bacteremia were randomized from 48 centers in the US and Europe. In the ITT population, 120 patients received daptomycin for injection and 115 received comparator (62 received an anti-staphylococcal semi synthetic penicillin and 53 received vancomycin). Thirty-five patients treated with an anti-staphylococcal semi-synthetic penicillin received vancomycin initially for 1 to 3 days, pending final susceptibility results for the S. aureus isolates. The median age among the 235 patients in the ITT population was 53 years (range: 21 to 91 years); 30/120 (25%) in the daptomycin for injection group and 37/115 (32%) in the comparator group were ≥65 years of age. Of the 235 ITT patients, there were 141 (60%) males and 156 (66%) Caucasians across the two treatment groups. In addition, 176 (75%) of the ITT population had systemic inflammatory response syndrome (SIRS) at baseline and 85 (36%) had surgical procedures within 30 days prior to onset of the S. aureus bacteremia. Eighty-nine patients (38%) had bacteremia caused by methicillin-resistant S. aureus (MRSA). Entry diagnosis was based on the modified Duke criteria and comprised 37 (16%) Definite, 144 (61%) Possible, and 54 (23%) Not Endocarditis. Of the 37 patients with an entry diagnosis of Definite Endocarditis, all (100%) had a final diagnosis of infective endocarditis, and of the 144 patients with an entry diagnosis of Possible Endocarditis, 15 (10%) had a final diagnosis of infective endocarditis as assessed by the Adjudication Committee. Of the 54 patients with an entry diagnosis of Not Endocarditis, 1 (2%) had a final diagnosis of infective endocarditis as assessed by the Adjudication Committee.

In the ITT population, there were 182 patients with bacteremia and 53 patients with infective endocarditis as assessed by the Adjudication Committee, including 35 with right-sided endocarditis and 18 with left-sided endocarditis. The 182 patients with bacteremia comprised 121 with complicated S. aureus bacteremia and 61 with uncomplicated S. aureus bacteremia.

Complicated bacteremia was defined as S. aureus isolated from blood cultures obtained on at least 2 different calendar days, and/or metastatic foci of infection (deep tissue involvement), and classification of the patient as not having endocarditis according to the modified Duke criteria. Uncomplicated bacteremia was defined as S. aureus isolated from blood culture(s) obtained on a single calendar day, no metastatic foci of infection, no infection of prosthetic material, and classification of the patient as not having endocarditis according to the modified Duke criteria. The definition of right-sided infective endocarditis (RIE) used in the clinical trial was Definite or Possible Endocarditis according to the modified Duke criteria and no echocardiographic evidence of predisposing pathology or active involvement of either the mitral or aortic valve. Complicated RIE comprised patients who were not intravenous drug users, had a positive blood culture for MRSA, serum creatinine ≥2.5 mg/dL, or evidence of extrapulmonary sites of infection. Patients who were intravenous drug users, had a positive blood culture for methicillin-susceptible S. aureus (MSSA), had serum creatinine <2.5 mg/dL, and were without evidence of extrapulmonary sites of infection were considered to have uncomplicated RIE.

The coprimary efficacy endpoints in the trial were the Adjudication Committee success rates at the Test of Cure visit (6 weeks after the last treatment dose) in the ITT and Per Protocol (PP) populations. The overall Adjudication Committee success rates in the ITT population were 44.2% (53/120) in patients treated with daptomycin for injection and 41.7% (48/115) in patients treated with comparator (difference = 2.4% [95% CI−10.2, 15.1]). The success rates in the PP population were 54.4% (43/79) in patients treated with daptomycin for injection and 53.3% (32/60) in patients treated with comparator (difference = 1.1% [95% CI−15.6, 17.8]).

Adjudication Committee success rates are shown in Table 11.

Table 11: Adjudication Committee Success Rates at Test of Cure in the S. aureus Bacteremia/Endocarditis Trial in Adult Patients (Population: ITT)
Population | Success Rate n/N (%) |  | Difference: Daptomycin for Injection-Comparator (Confidence Interval)
Population | Daptomycin for Injection 6 mg/kg | Comparator [Comparator: vancomycin (1 g IV every 12h) or an anti-staphylococcal semi-synthetic penicillin (i.e., nafcillin, oxacillin, cloxacillin, or flucloxacillin; 2 g IV every 4h), each with initial low-dose gentamicin.] | Difference: Daptomycin for Injection-Comparator (Confidence Interval)
Overall | 53/120 (44%) | 48/115 (42%) | 2.4% (-10.2, 15.1) [95% Confidence Interval.]
Baseline Pathogen
Methicillin-susceptible S. aureus | 33/74 (45%) | 34/70 (49%) | -4.0% (-22.6, 14.6) [97.5% Confidence Interval (adjusted for multiplicity).]
Methicillin-resistant S. aureus | 20/45 (44%) | 14/44 (32%) | 12.6% (-10.2, 35.5)
Entry Diagnosis [According to the modified Duke criteria^5.]
Definite or Possible Infective Endocarditis | 41/90 (46%) | 37/91 (41%) | 4.9% (-11.6, 21.4)
Not Infective Endocarditis | 12/30 (40%) | 11/24 (46%) | -5.8% (-36.2, 24.5)
Final Diagnosis
Uncomplicated Bacteremia | 18/32 (56%) | 16/29 (55%) | 1.1% (-31.7, 33.9) [99% Confidence Interval (adjusted for multiplicity).]
Complicated Bacteremia | 26/60 (43%) | 23/61 (38%) | 5.6% (-17.3, 28.6)
Right-Sided Infective Endocarditis | 8/19 (42%) | 7/16 (44%) | -1.6% (-44.9, 41.6)
Uncomplicated Right-Sided Infective Endocarditis | 3/6 (50%) | 1/4 (25%) | 25.0% (-51.6, 100.0)
Complicated Right-Sided Infective Endocarditis | 5/13 (39%) | 6/12 (50%) | -11.5% (-62.4, 39.4)
Left-Sided Infective Endocarditis | 1/9 (11%) | 2/9 (22%) | -11.1% (-55.9, 33.6)

Eighteen (18/120) patients in the daptomycin for injection arm and 19/116 patients in the comparator arm died during the trial. These comprise 3/28 daptomycin for injection-treated patients and 8/26 comparator-treated patients with endocarditis, as well as 15/92 daptomycin for injection-treated patients and 11/90 comparator-treated patients with bacteremia. Among patients with persisting or relapsing S. aureus infections, 8/19 daptomycin for injection-treated patients and 7/11 comparator-treated patients died.

Overall, there was no difference in time to clearance of S. aureus bacteremia between daptomycin for injection and comparator. The median time to clearance in patients with MSSA was 4 days and in patients with MRSA was 8 days.

Failure of treatment due to persisting or relapsing S. aureus infections was assessed by the Adjudication Committee in 19/120 (16%) daptomycin for injection-treated patients (12 with MRSA and 7 with MSSA) and 11/115 (10%) comparator-treated patients (9 with MRSA treated with vancomycin and 2 with MSSA treated with an anti-staphylococcal semi-synthetic penicillin). Among all failures, isolates from 6 daptomycin for injection-treated patients and 1 vancomycin-treated patient developed increasing MICs (reduced susceptibility) by central laboratory testing during or following therapy. Most patients who failed due to persisting or relapsing S. aureus infection had deep-seated infection and did not receive necessary surgical intervention [see Warnings and Precautions (5.9)].

15 REFERENCES

1. Liu SL, Howard LC, Van Lier RBL, Markham JK: Teratology studies with daptomycin administered intravenously (iv) to rats and rabbits. Teratology 37(5):475, 1988.
2. Stroup JS, Wagner J, Badzinski T: Use of daptomycin in a pregnant patient with Staphylococcus aureus endocarditis. Ann Pharmacother 44(4):746–749, 2010.
3. Buitrago MI, Crompton JA, Bertolami S, North DS, Nathan RA. Extremely low excretion of daptomycin into breast milk of a nursing mother with methicillin-resistant Staphylococcus aureus pelvic inflammatory disease. Pharmacotherapy 2009;29(3):347–351.
4. Klibanov OM, Vickery S, Nortey C: Successful treatment of infective panniculitis with daptomycin in a pregnant, morbidly obese patient. Ann Pharmacother 48(5):652–655, 2014.
5. Li JS, Sexton DJ, Mick N, Nettles R, Fowler VG Jr, Ryan T, Bashore T, Corey GR. Proposed modifications to the Duke criteria for the diagnosis of infective endocarditis. Clin Infect Dis 2000;30:633–638.

16 HOW SUPPLIED/STORAGE AND HANDLING

Daptomycin for Injection is supplied as a sterile pale yellow to light brown lyophilized cake in a single-dose vial containing either 350 mg or 500 mg of daptomycin:

Unit of Sale | Strength
NDC 0409-0120-01 Carton containing 1 single-dose vial | 350 mg/vial
NDC 0409-0122-01 Carton containing 1 single-dose vial | 500 mg/vial

STORAGE AND HANDLING

Store original packages at 2°C to 25°C (36°F to 77°F); do not freeze. Brief exposure to 30°C (86°F) permitted [see USP Controlled Room Temperature] [see Dosage and Administration (2.5)]. Storage conditions for the reconstituted and diluted solutions are described in another section of the prescribing information [see Dosage and Administration (2.5)].

The vial stopper is not made with natural rubber latex.

17 PATIENT COUNSELING INFORMATION

Allergic Reactions

Advise patients that allergic reactions, including serious skin, kidney, lung, or other organ reactions, could occur and that these serious reactions require immediate treatment. Patients should report any previous allergic reactions to daptomycin [see Warnings and Precautions (5.1, 5.4, 5.5)].

Muscle Pain or Weakness (Myopathy and Rhabdomyolysis, Peripheral Neuropathy)

Advise patients to report muscle pain or weakness, especially in the forearms and lower legs, as well as tingling or numbness [see Warnings and Precautions (5.2, 5.6)].

Cough, Breathlessness or Fever (Eosinophilic Pneumonia)

Advise patients to report any symptoms of cough, breathlessness, or fever [see Warnings and Precautions (5.3)].

C. difficile-Associated Diarrhea (CDAD)

Advise patients that diarrhea is a common problem caused by antibacterials, including Daptomycin for Injection that usually ends when the antibacterial is discontinued. Sometimes after starting treatment with antibacterials, including Daptomycin for Injection, patients can develop watery and bloody stools (with or without stomach cramps and fever), even as late as 2 or more months after having received the last dose of the antibacterial. If this occurs, patients should contact their physician as soon as possible [see Warnings and Precautions (5.8)],

Antibacterial Resistance

Patients should be counseled that antibacterial drugs, including Daptomycin for Injection, should be used to treat bacterial infections. They do not treat viral infections (e.g., the common cold). When Daptomycin for Injection is prescribed to treat a bacterial infection, patients should be told that although it is common to feel better early in the course of therapy, the medication should be administered exactly as directed. Skipping doses or not completing the full course of therapy may (1) decrease the effectiveness of the immediate treatment and (2) increase the likelihood that bacteria will develop resistance and will not be treatable by Daptomycin for Injection or other antibacterial drugs in the future.

Distributed by Hospira, Inc., Lake Forest, IL 60045 USA

LAB-1007-4.0

PRINCIPAL DISPLAY PANEL - 500 mg Vial Label

NDC 0409-0122-01

Daptomycin
for Injection

500 mg per vial

Must be reconstituted
For Intravenous Use

Single dose vial - Discard Unused Portion

PRINCIPAL DISPLAY PANEL - 500 mg Vial Carton

NDC 0409-0122-01
Rx only

Daptomycin
for Injection

500 mg per vial

For Intravenous Use

Use 0.9% Sodium Chloride
Injection, USP for
reconstitution only.

Single-dose vial -
Discard unused portion

Hospira

PRINCIPAL DISPLAY PANEL - 350 mg Vial Label

NDC 0409-0120-01

Daptomycin
for Injection

350 mg per vial

Must be reconstituted
For Intravenous Use

Single dose vial - Discard Unused Portion

PRINCIPAL DISPLAY PANEL - 350 mg Vial Carton

NDC 0409-0120-01
Rx only

Daptomycin
for Injection

350 mg per vial

For Intravenous Use

Use 0.9% Sodium Chloride
Injection, USP for
reconstitution only.

Single-dose vial -
Discard unused portion

Hospira